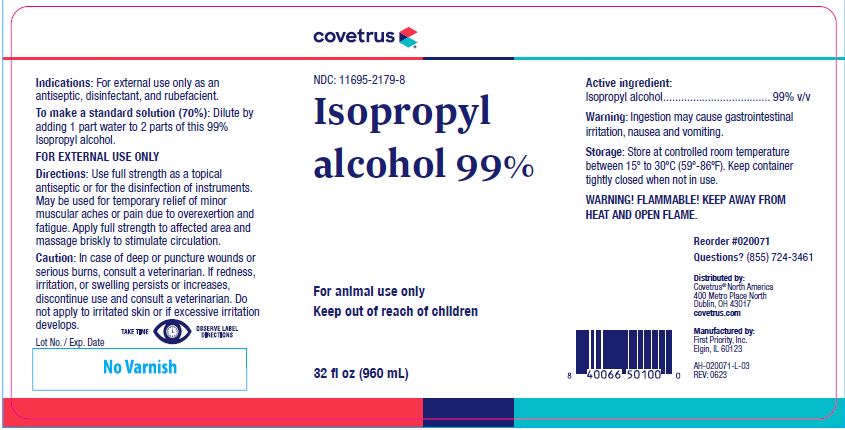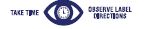 DRUG LABEL: Isopropyl Alcohol
NDC: 11695-2179 | Form: LIQUID
Manufacturer: Butler Animal health Supply, LLC dba Covetrus North America
Category: animal | Type: OTC ANIMAL DRUG LABEL
Date: 20260120

ACTIVE INGREDIENTS: ISOPROPYL ALCOHOL 0.77 g/1 mL

Isopropyl alcohol 99%

KEEP OUT OF REACH OF CHILDREN

For animal use only
Keep out of reach of children

Indications:

For external use only as an antiseptic, disinfectant, and rubefacient.

To Make A Standard Solution (70%):

Dilute by adding 1 part water to 2 parts of this 99% Isopropyl Alcohol.
FOR EXTERNAL USE ONLY

Directions:

Use full strength as a topical antiseptic or for the disinfection of instruments. May be used for temporary relief of minor muscular aches or pain due to overexertion and fatigue. Apply full strength to affected area and massage briskly to stimulate circulation.

CAUTION:

In case of deep or puncture wounds or serious burns, consult a veterinarian. If redness, irritation, or swelling persists or increases, discontinue use and consult a veterinarian. Do not apply to irritated skin or if excessive irritation develops.

Active Ingredient:

Isopropyl alcohol.................................... 99% v/v

Warning:

Ingestion may cause gastrointestinal irritation, nausea and vomiting.

Storage:

Store at controlled room temperature between 15º to 30ºC (59º-86ºF). Keep container tightly closed when not in use.

WARNING! FLAMMABLE! KEEP AWAY FROM HEAT AND OPEN FLAME.

HOW SUPPLIED

32 fl oz (960 mL)

INFORMATION FOR OWNERS/CAREGIVERS

Reorder #020071

Questions? (855) 724-3461

Distributed by:Covetrus® North America
400 Metro Place North
Dublin, OH 43017
covetrus.com

Manufactured by:
First Priority, Inc.
Elgin, IL 60123

AH-020071-L-03
REV: 0623